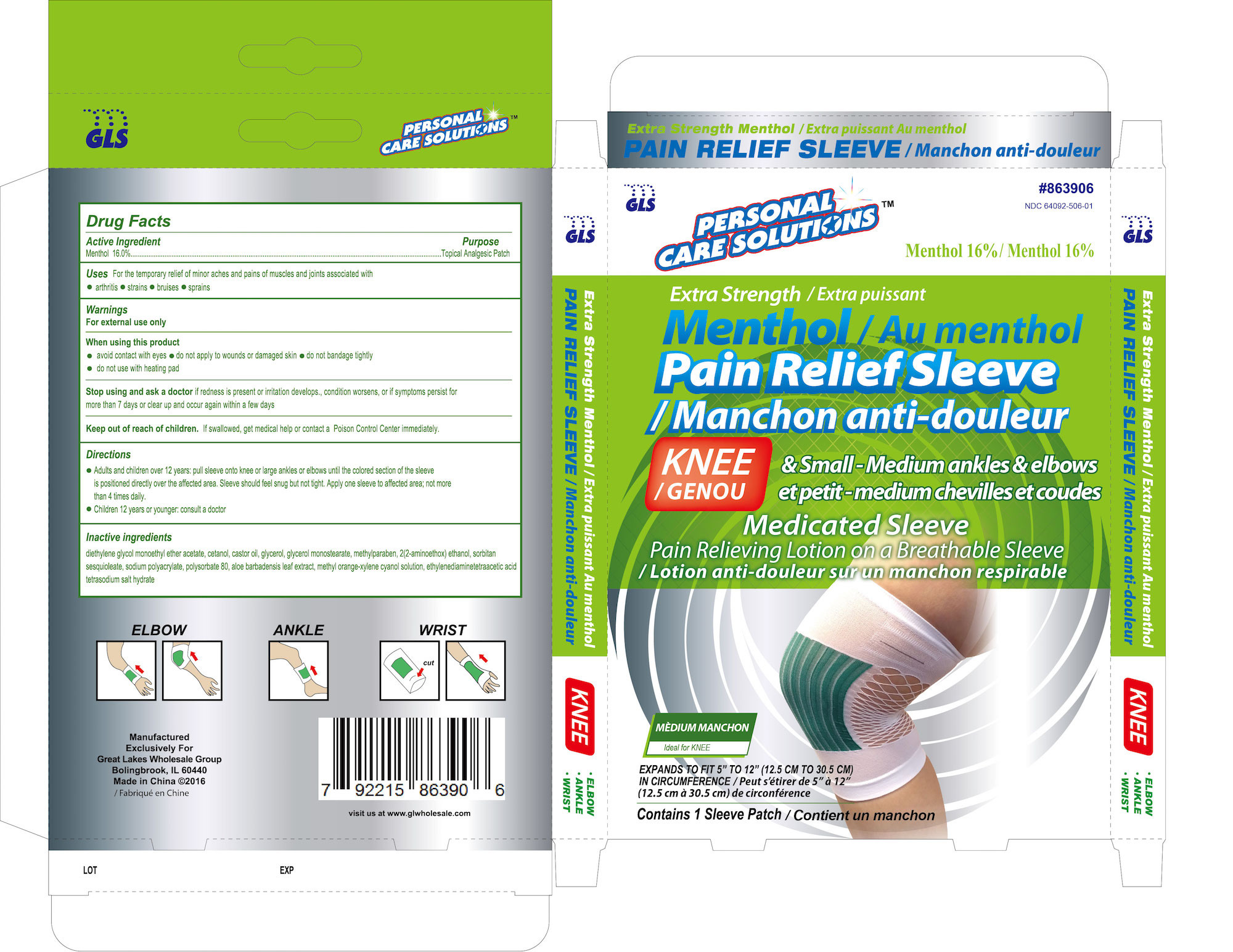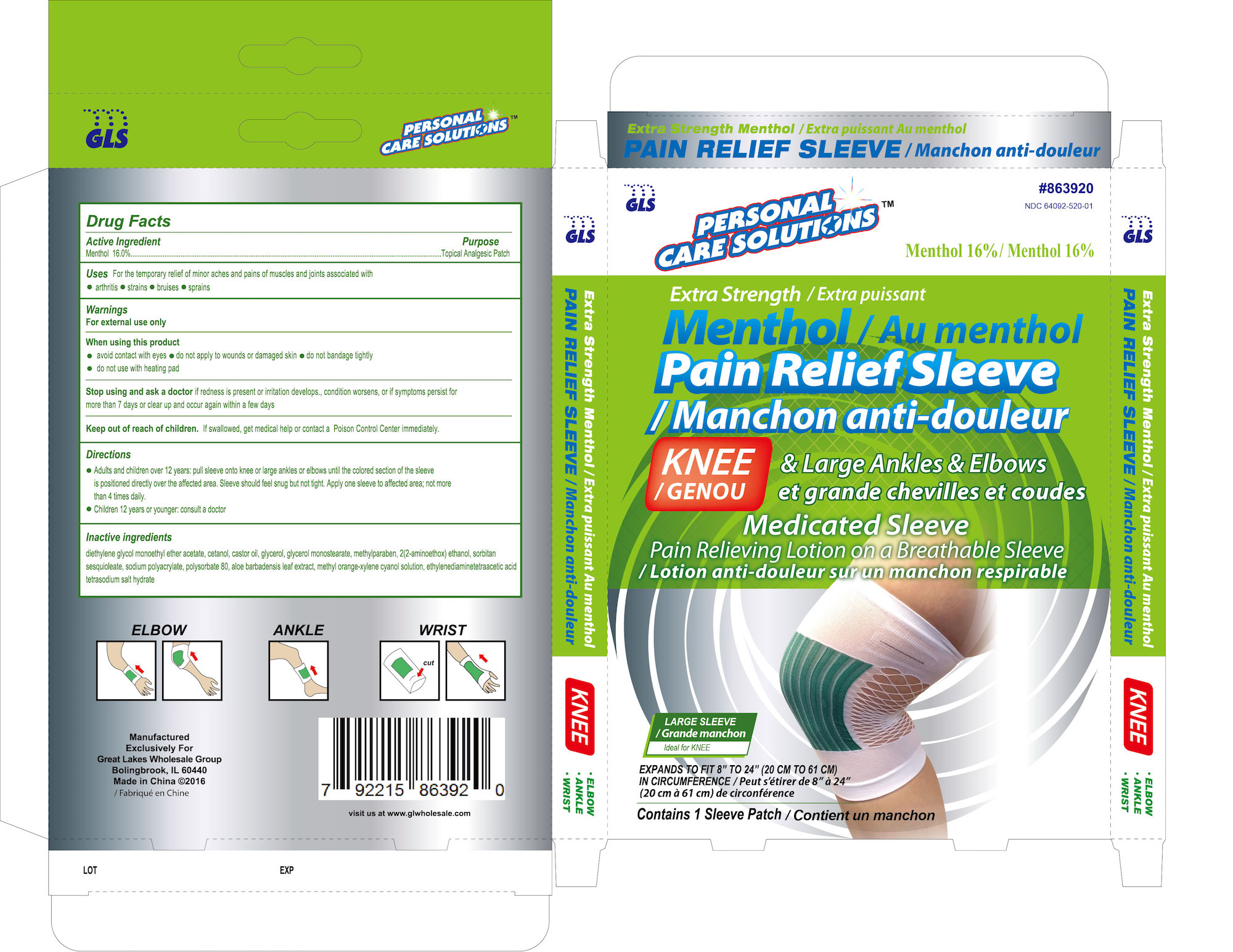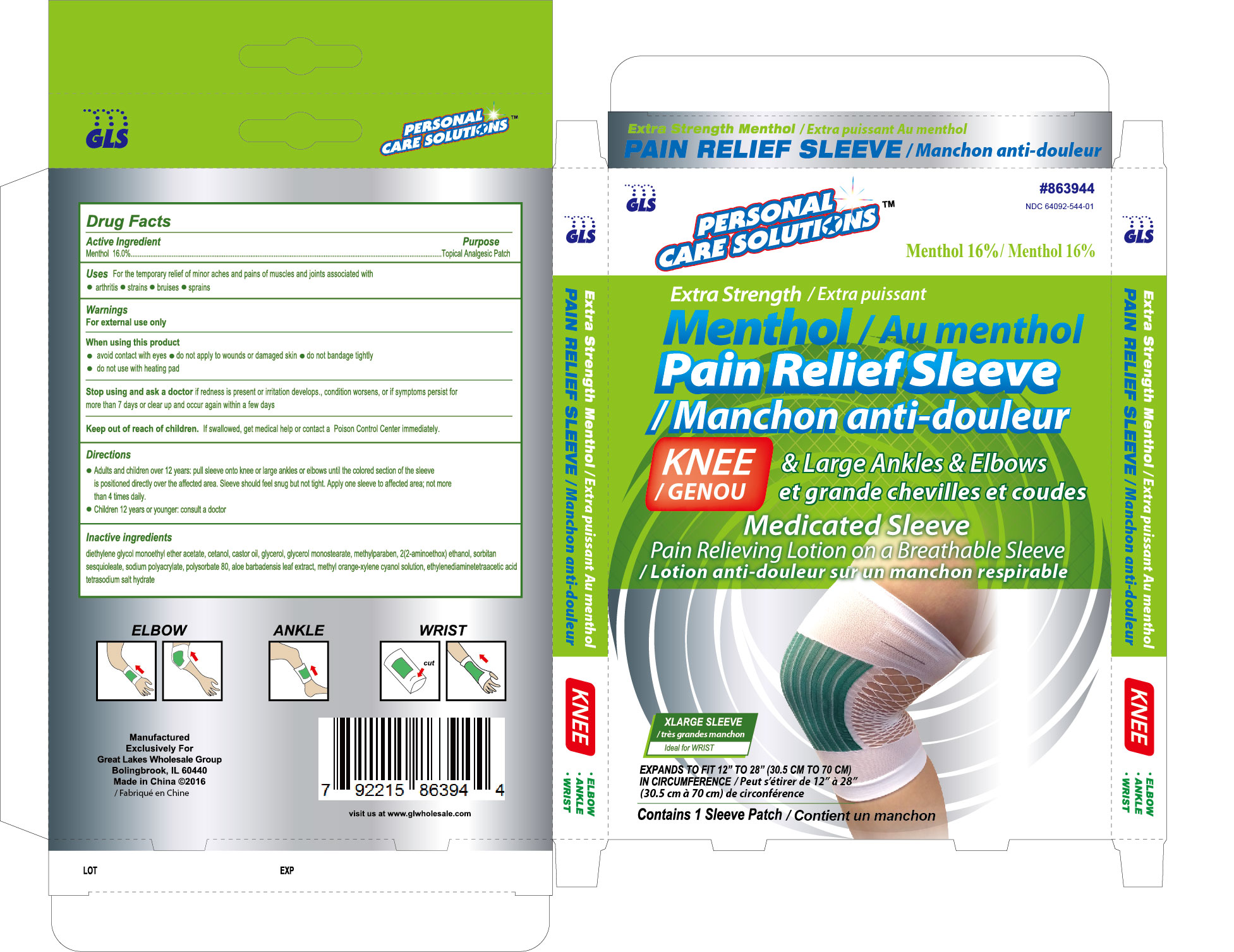 DRUG LABEL: Pain Relief Sleeve
NDC: 64092-520 | Form: PATCH
Manufacturer: Great Lakes Wholesale, Marketing, and Sales, Inc
Category: otc | Type: HUMAN OTC DRUG LABEL
Date: 20161205

ACTIVE INGREDIENTS: MENTHOL 160 mg/1 mL
INACTIVE INGREDIENTS: GLYCERYL MONOSTEARATE; METHYLPARABEN; SORBITAN SESQUIOLEATE; SODIUM POLYACRYLATE (2500000 MW); POLYSORBATE 80; DIETHYLENE GLYCOL MONOETHYL ETHER; CETYL ALCOHOL; MONOETHANOLAMINE; ALOE VERA LEAF; METHYL ORANGE; EDETIC ACID; SOLASULFONE

ACTIVE INGREDIENT

Menthol 16.0%

PURPOSE

Topical Analgesic Patch

INDICATIONS AND USAGE

For temporary relief of minor aches and pains of muscles and joints associated with:

- arthritis
- strains
- bruises
- sprains

WARNINGS

For external use only

When using this product:

- avoid contact with eyes
- do not apply to wounds or damaged skin
- do not bandage tightly
- do not use with heating pad

Stop using and ask a doctor

if redness is present or irritation develops. Condition worsens, or if symptioms persist for more than 7 days or clear up and occur again within a few days.

KEEP OUT OF REACH OF CHILDREN

If swallowed, get medical help or contact a Poison Control Center immediately

INSTRUCTIONS FOR USE

- Adults and children over 12 years: pull sleeve onto knee or large ankles or elbows until the colored section of the sleeve is positioned directly over the affected area. Sleeve should feel snug, but not tight.
- Children 12 years or younger: consult a doctor

INACTIVE INGREDIENT

diethylene glycol monoethyl ether acetate, cetanol, glycerol, glycerol monostearate, methylparaben, 2(2-aminoethoxy) ethanol, sorbitan sesquiolate, sodium polyacrylate, polysorbate 80, aloe barbadensis leaf extract, methyl orange-xylene cyanol solution, ethylenediaminetetracetic acid tetrasodium salt hydrate.

DESCRIPTION

NDC 64092-506-1, ITEM 863906

GLS

Personal Care Solutions

Extra Strength

Menthol 16%

Pain Relief Sleeve

KNEE & Small-Medium ankles & elbows

Medicated Sleeve

Pain relieving Lotion on a Breathable Sleeve

Medium

Ideal for KNEE

EXPANDS TO FIT 5" TO 12" (12.5cm to 30.5cm)

IN CIRCUMFERENCE

Contains 1 Sleeve Patch

KNEE

- ELBOT
- ANKLE
- WRIST

NDC 64092-520-1, ITEM 863920

GLS

Personal Care Solutions

Extra Strength

Menthol 16%

Pain Relief Sleeve

KNEE & Large Ankles & Elbows

Medicated Sleeve

Pain relieving Lotion on a Breathable Sleeve

Large Sleeve

Ideal for KNEE

EXPANDS TO FIT 8" TO 24" (20 CM TO 61 CM)

IN CIRCUMFERENCE

Contains 1 Sleeve Patch

KNEE

- ELBOW
- ANKLE
- WRIST

NDC 64092-520-1, ITEM 863920

GLS

Personal Care Solutions

Extra Strength

Menthol 16%

Pain Relief Sleeve

KNEE & Large Ankles & Elbows

Medicated Sleeve

Pain relieving Lotion on a Breathable Sleeve

XLarge Sleeve

Ideal for KNEE

EXPANDS TO FIT 12" TO 28" (30.5 CM to 70 CM)

IN CIRCUMFERENCE

Contains 1 Sleeve Patch

KNEE

ELBOW
ANKLE
WRIST

DOSAGE AND ADMINISTRATION

Adults and children over 12 years: pull sleeve onto knee or large ankle or elbow until the colored section of the sleeve is positioned directly over the affected area. sleeve should feel snug, but not tight.